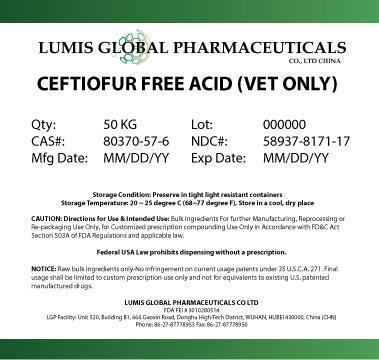 DRUG LABEL: CEFTIOFUR FREE ACID
NDC: 58937-8171 | Form: POWDER
Manufacturer: LUMIS GLOBAL PHARMACEUTICALS CO LTD
Category: other | Type: BULK INGREDIENT
Date: 20140320

ACTIVE INGREDIENTS: CEFTIOFUR 1 g/1 g

CEFTIOFUR FREE ACID